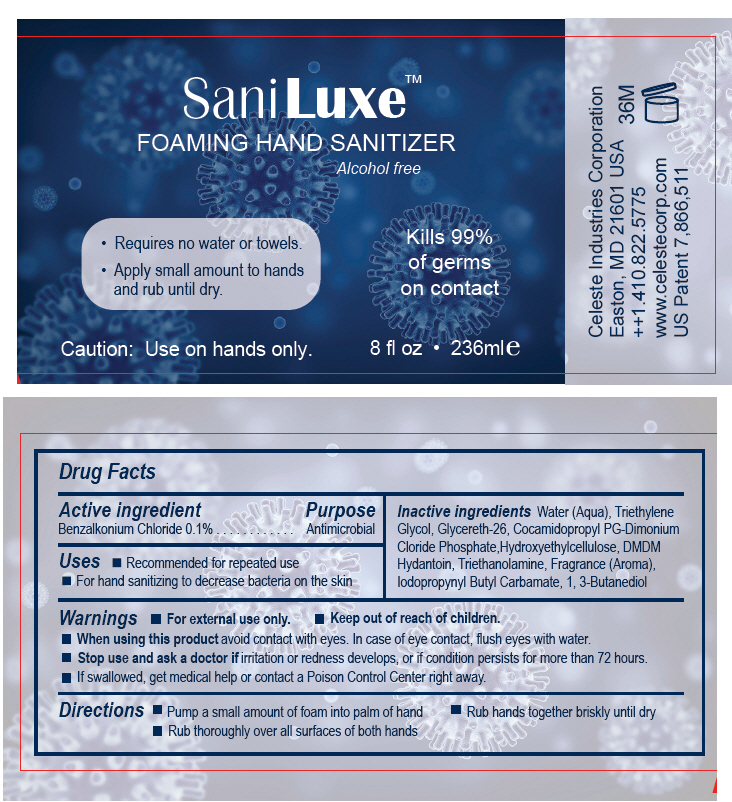 DRUG LABEL: Sani Luxe Foaming Hand Sanitizer Alcohol Free
NDC: 71489-006 | Form: LIQUID
Manufacturer: Celeste Industries Corporation
Category: otc | Type: HUMAN OTC DRUG LABEL
Date: 20240708

ACTIVE INGREDIENTS: BENZALKONIUM CHLORIDE 1 mg/1 mL
INACTIVE INGREDIENTS: WATER; TRIETHYLENE GLYCOL; GLYCERETH-26; COCAMIDOPROPYL PROPYLENE GLYCOL-DIMONIUM CHLORIDE PHOSPHATE; HYDROXYETHYL CELLULOSE (5000 MPA.S AT 1%); DMDM HYDANTOIN; TROLAMINE; IODOPROPYNYL BUTYLCARBAMATE; BUTYLENE GLYCOL

SaniLuxe™ Foaming Hand Sanitizer Alcohol Free

Drug Facts

Active ingredient

Benzalkonium Chloride 0.1%

Purpose

Antimicrobial

Uses

- Recommended for repeated use
- For hand sanitizing to decrease bacteria on the skin

Warnings

- For external use only.

- Keep out of reach of children.

- When using this product avoid contact with eyes. In case of eye contact, flush eyes with water.

- Stop use and ask a doctor if irritation or redness develops, or if condition persists for more than 72 hours.
- If swallowed, get medical help or contact a Poison Control Center right away.

Directions

- Pump a small amount of foam into palm of hand
- Rub hands together briskly until dry
- Rub thoroughly over all surfaces of both hands

Inactive ingredients

Water (Aqua), Triethylene Glycol, Glycereth-26, Cocamidopropyl PG-Dimonium Cloride Phosphate,Hydroxyethylcellulose, DMDM Hydantoin, Triethanolamine, Fragrance (Aroma), Iodopropynyl Butyl Carbamate, 1, 3-Butanediol

PACKAGE LABEL

SaniLuxe™

FOAMING HAND SANITIZER

Alcohol free

- Requires no water or towels.
- Apply small amount to hands
  and rub until dry.

Kills 99%
of germs
on contact

Caution: Use on hands only.

8 fl oz • 236ml e